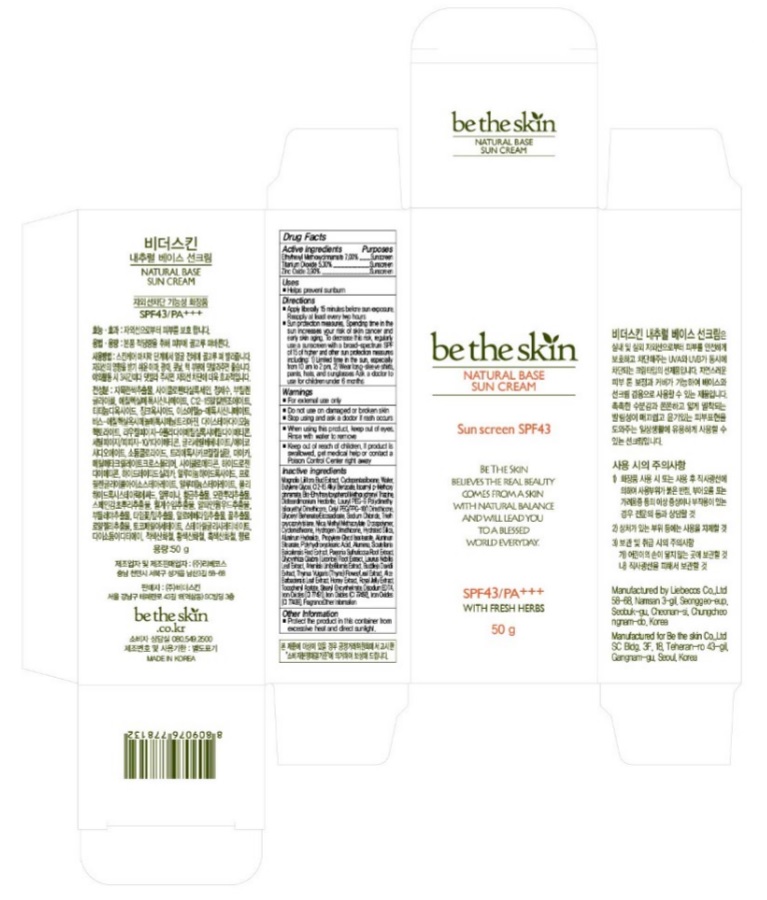 DRUG LABEL: BE THE SKIN NATURAL BASE SUN
NDC: 72802-001 | Form: CREAM
Manufacturer: BETHESKIN Co.,Ltd
Category: otc | Type: HUMAN OTC DRUG LABEL
Date: 20190213

ACTIVE INGREDIENTS: OCTINOXATE 0.07 g/1 g; TITANIUM DIOXIDE 0.053 g/1 g; ZINC OXIDE 0.039 g/1 g
INACTIVE INGREDIENTS: MAGNOLIA LILIIFLORA WHOLE; CYCLOMETHICONE 5; WATER; ALKYL (C12-15) BENZOATE; BUTYLENE GLYCOL; BEMOTRIZINOL; AMILOXATE; DISTEARDIMONIUM HECTORITE; LAURYL PEG-9 POLYDIMETHYLSILOXYETHYL DIMETHICONE; PAEONIA X SUFFRUTICOSA ROOT; GLYCYRRHIZA GLABRA; SCUTELLARIA BAICALENSIS ROOT; CETYL PEG/PPG-10/1 DIMETHICONE (HLB 3); CYCLOMETHICONE; SODIUM CHLORIDE; ALUMINUM OXIDE; ALUMINUM STEARATE; ALUMINUM HYDROXIDE; POLYHYDROXYSTEARIC ACID (2300 MW); GLYCERYL BEHENATE/EICOSADIOATE; HYDROGEN DIMETHICONE (13 CST); HYDRATED SILICA; ROYAL JELLY; MICA; STEARYL GLYCYRRHETINATE; .ALPHA.-TOCOPHEROL ACETATE; TRIETHOXYCAPRYLYLSILANE; METHYL METHACRYLATE/GLYCOL DIMETHACRYLATE CROSSPOLYMER; EDETATE DISODIUM

72802_001

ACTIVE INGREDIENT

Octinoxate 7.00%
Titanium Dioxide 5.30%
Zinc Oxide 3.90%

PURPOSE

Sunscreen

INDICATIONS AND USAGE

Helps prevent sunburn

DOSAGE AND ADMINISTRATION

Apply liberally 15 minutes before sun exposure. Reapply at least every two hours

WARNINGS

For external use only.
Do not use on damaged or broken skin.
When using this product, keep out of eyes. Rinse with water to remove.
Stop using and ask a doctor if rash occurs.

KEEP OUT OF REACH OF CHILDREN

Keep out of reach of the children. If product is swallowed, get medical help or contact a poison control center right away.

INACTIVE INGREDIENT

Magnolia Liliflora Bud Extract, Cyclopentasiloxane, Water, Butylene Glycol, C12-15 Alkyl Benzoate, Isoamyl p-Methoxycinnamate, Bis-Ethylhexyloxyphenol Methoxyphenyl Triazine, Disteardimonium Hectorite, Lauryl PEG-9 Polydimethylsiloxyethyl Dimethicone, Cetyl PEG/PPG-10/1 Dimethicone, Glyceryl Behenate/Eicosadioate, Sodium Chloride, Triethoxycaprylylsilane, Mica, Methyl Methacrylate Crosspolymer, Cyclomethicone, Hydrogen Dimethicone, Hydrated Silica, Aluminum Hydroxide, Propylene Glycol Isostearate, Aluminum Stearate, Polyhydroxystearic Acid, Alumina, Scutellaria Baicalensis Root Extract, Paeonia Suffruticosa Root Extract, Glycyrrhiza Glabra (Licorice) Root Extract, Laurus Nobilis Leaf Extract, Artemisia Umbelliformis Extract, Buddleja Davidii Extract, Thymus Vulgaris (Thyme) Flower/Leaf Extract, Aloe Barbadensis Leaf Extract, Honey Extract, Royal Jelly Extract, Tocopheryl Acetate, Stearyl Glycyrrhetinate, Disodium EDTA, Iron Oxides (CI 77491), Iron Oxides (CI 77492), Iron Oxides (CI 77499), Fragrance